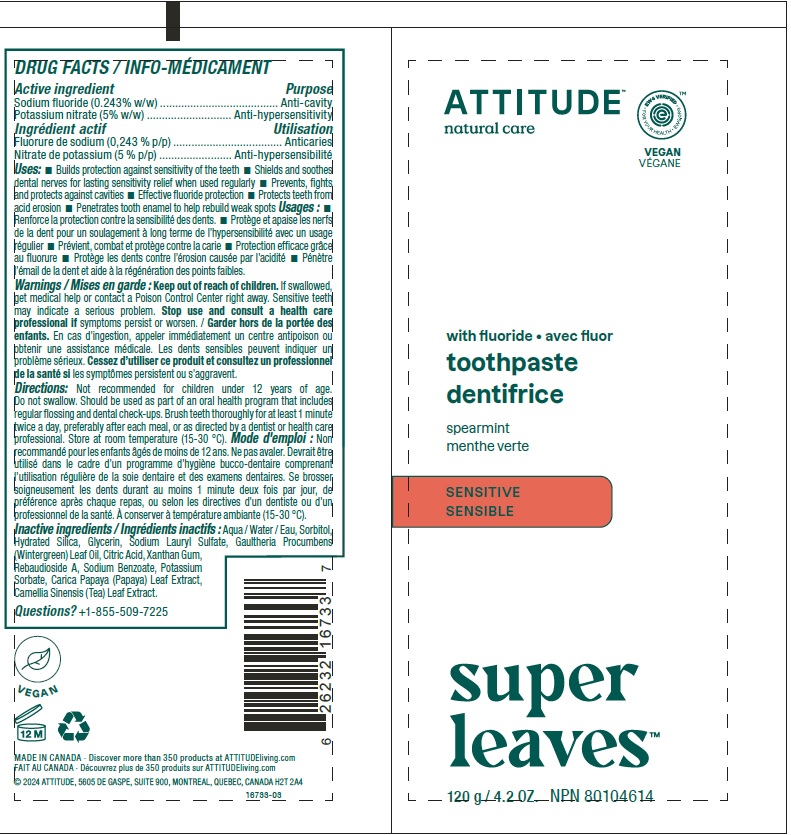 DRUG LABEL: BIO SPECTRA
NDC: 61649-733 | Form: PASTE, DENTIFRICE
Manufacturer: 9055-7588 Quebec Inc. DBA Attitude
Category: otc | Type: HUMAN OTC DRUG LABEL
Date: 20240426

ACTIVE INGREDIENTS: SODIUM FLUORIDE 0.243 g/100 g; POTASSIUM NITRATE 5 g/100 g
INACTIVE INGREDIENTS: WATER; SORBITOL; HYDRATED SILICA; GLYCERIN; SODIUM LAURYL SULFATE; METHYL SALICYLATE; XANTHAN GUM; ANHYDROUS CITRIC ACID; REBAUDIOSIDE A; SODIUM BENZOATE; CARICA PAPAYA LEAF; GREEN TEA LEAF; POTASSIUM SORBATE

ATTITUDE Super Leaves Toothpaste with fluoride - Sensitive

DRUG FACTS

ACTIVE INGREDIENT

Active ingredients | Purpose
Sodium fluoride (0.243% w/w) | Anti-cavity
Potassium nitrate (5% w/w) | Anti-hypersensitivity

Uses

- Builds protection against sensitivity of the teeth.
- Shields and soothes dental nerves for lasting sensitivity relief when used regularly.
- Prevents, fights and protects against cavities.
- Effective fluoride protection.
- Protects teeth from acid erosion.
- Penetrates tooth enamel to help rebuild weak spots.

Warnings

Keep out of reach of children.

If swallowed, call a poison control centre or get medical help right away.

STOP USE

Sensitive teeth may indicate a serious problem. Stop use and consult a health care professional ifsymptoms persist or worsen.

Directions

Do not swallow. Should be used as part of an oral health program that includes regular flossing and dental check-ups. Brush teeth thoroughly for at least 1 minute twice a day, preferably after each meal, or as directed by a dentist or health care professional. Not recommended for children under 12 years of age. Store at room temperature (15-30 °C).

Non-medicinal ingredients

Aqua / Water / Eau, Sorbitol, Hydrated Silica, Glycerin, Sodium Lauryl Sulfate, Gaultheria Procumbens (Wintergreen) Leaf Oil, Citric Acid, Xanthan Gum, Rebaudioside A, Sodium Benzoate, Potassium Sorbate, Carica Papaya (Papaya) Leaf Extract, Camellia Sinensis (Tea) Leaf Extract.

QUESTIONS?

+1-855-509-7225

PRINCIPAL DISPLAY PANEL - 120 g Tube Label

ATTITUDE®
natural care

EWG VERIFIED

Vegan

with fluoride

toothpaste
Spearmint

SENSITIVE

Super Leaves

NPN 80104614

120 g 4.2 OZ.